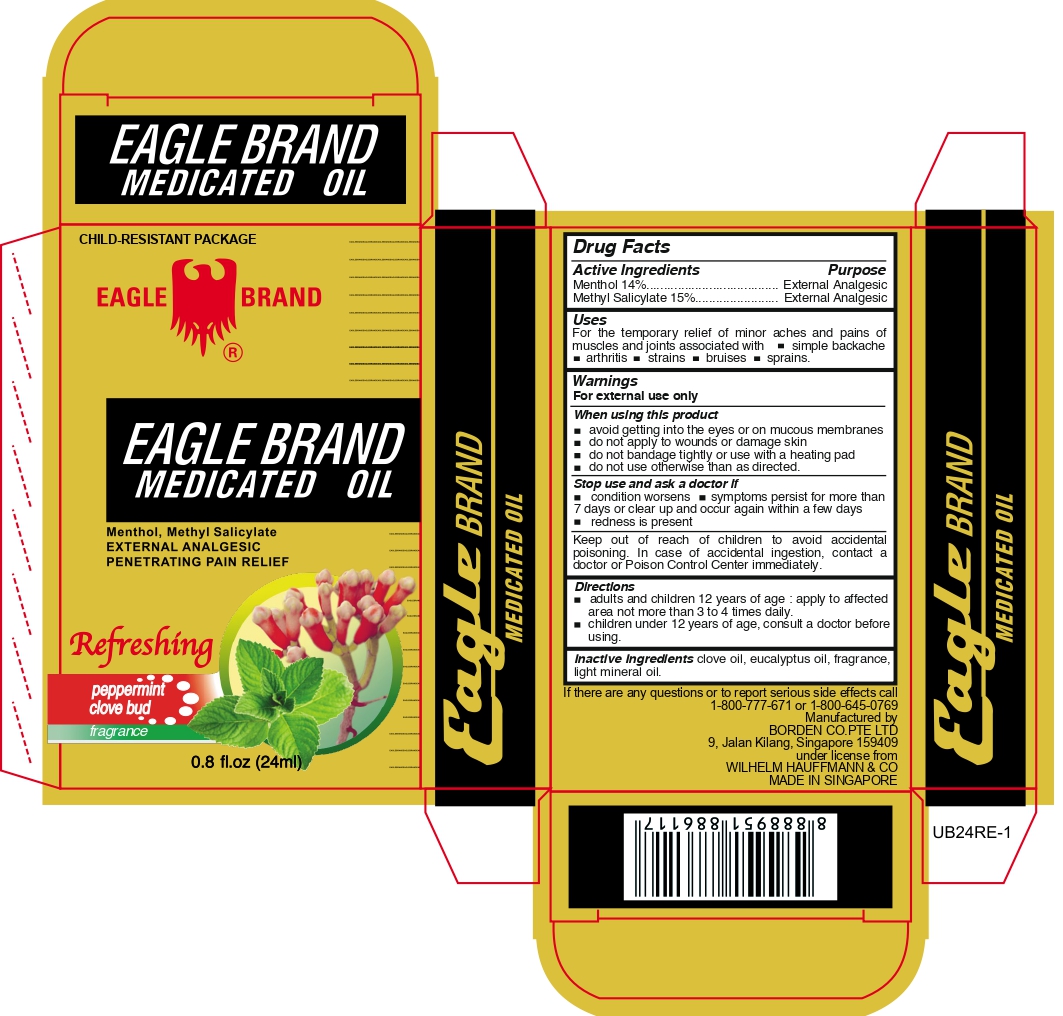 DRUG LABEL: Eagle Medicated Oil
NDC: 43405-102 | Form: OIL
Manufacturer: Borden Company (Private) Limited
Category: otc | Type: HUMAN OTC DRUG LABEL
Date: 20241002

ACTIVE INGREDIENTS: METHYL SALICYLATE 15 g/100 mL; MENTHOL 14 g/100 mL
INACTIVE INGREDIENTS: CLOVE OIL; LIGHT MINERAL OIL; EUCALYPTUS OIL

Refreshing External Analgesic OIl

Active Ingredients

Menthol 14%

Methyl Salicylate 15%

Purpose

External Analgesic

External Analgesic

Uses

For the temporary relief of minor pains and aches of muscles and joints associated with ■simple backache ■arthritis ■strains ■bruises ■ sprains

Warnings

For external use only

When using this product

■ avoid getting into the eyes or on mucous membranes

■ do not apply to wounds and damaged skin

■ do not bandage tightly or use with a heating pad

■ do not use otherwise tha as directed

Stop use and ask a doctor if

■ condition worsens, ■ symptoms persist for more than 7 days or clear up and occur again within a few days ■ redness is present

Keep out of reach of children to avoid accidental poisoning. In case of accidental ingestion contact a doctor or Poison Control Center immediately

Directions

■ adults and children 12 years of age: apply to affected area not more than 3 to 4 times daily. ■ children under 12 years of age, consult a doctor before using

Inactive Ingredients

clove oil, eucalyptus oil, fragrance, light mineral oil